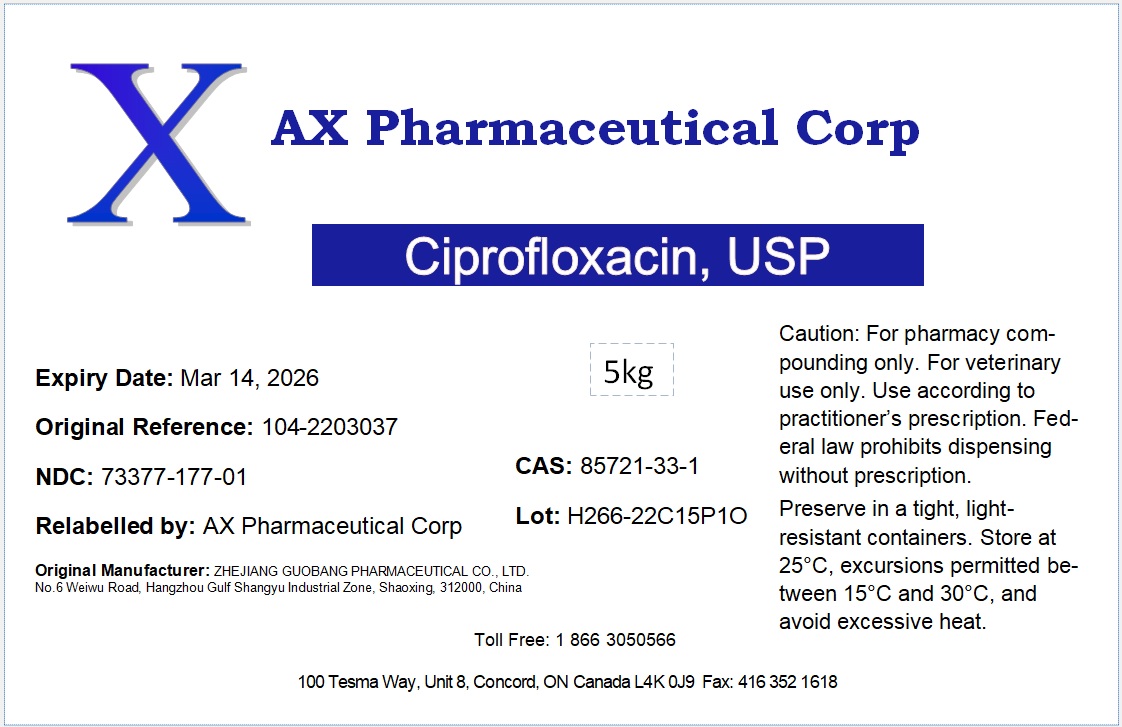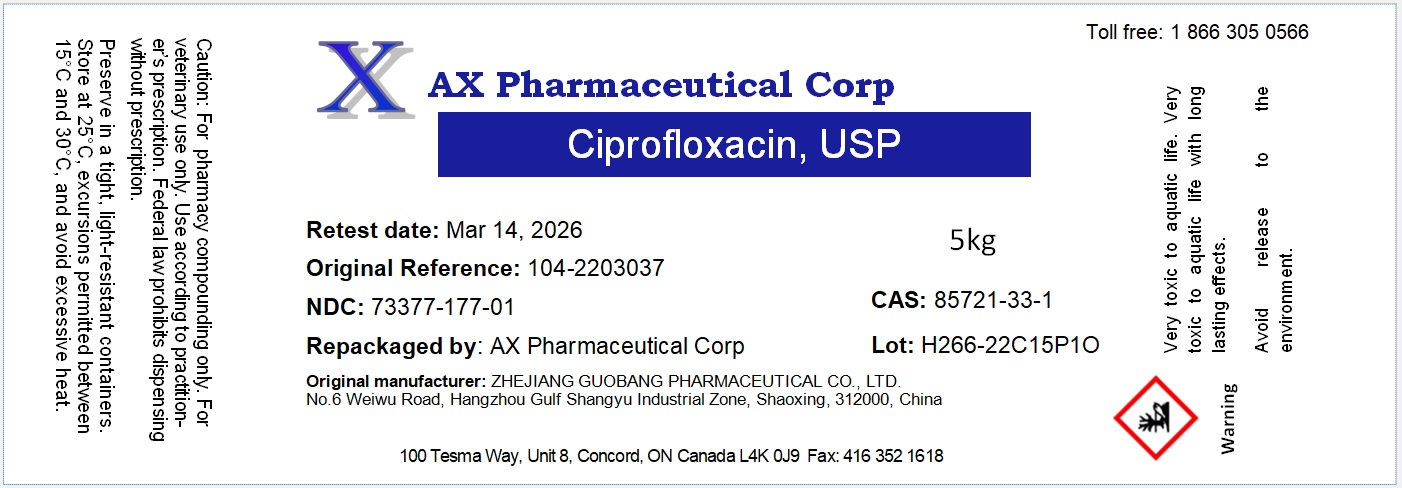 DRUG LABEL: Ciprofloxacin
NDC: 73377-177 | Form: POWDER
Manufacturer: AX Pharmaceutical Corp
Category: other | Type: BULK INGREDIENT - ANIMAL DRUG
Date: 20260119

ACTIVE INGREDIENTS: CIPROFLOXACIN 1 g/1 g

Ciprofloxacin